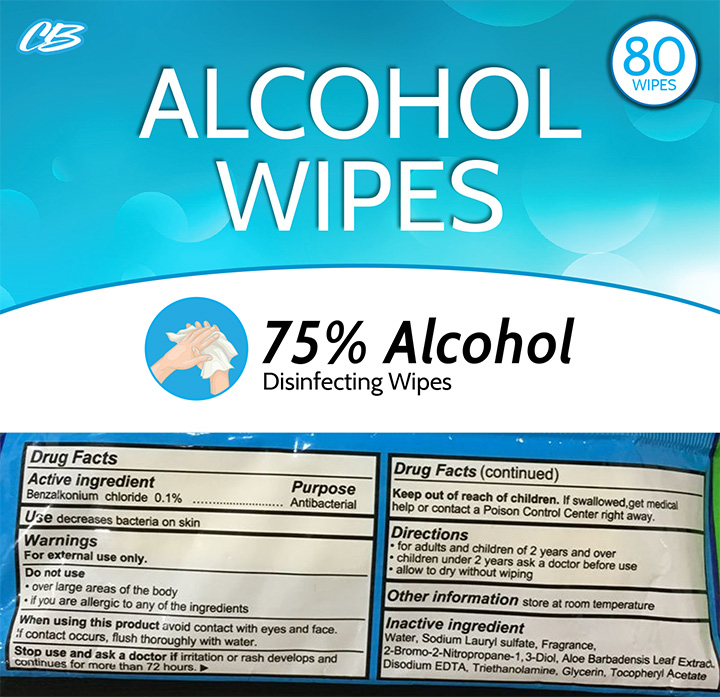 DRUG LABEL: CB Alcohol Wipes
NDC: 73529-352 | Form: SWAB
Manufacturer: Nutritech Pharmaceuticals, Inc
Category: otc | Type: HUMAN OTC DRUG LABEL
Date: 20200324

ACTIVE INGREDIENTS: BENZALKONIUM CHLORIDE 0.1 g/100 g
INACTIVE INGREDIENTS: ALOE VERA LEAF; .ALPHA.-TOCOPHEROL ACETATE; CUPRIC BIS(TRIETHANOLAMINE); 2-BROMO-2-NITROETHANOL; WATER; DISODIUM EDTA-COPPER; SODIUM LAURYL SULFATE; GLYCERIN

Active Ingredient

Benzalkonium chloride 0.1%

Purpose

Antibacterial

Use

decreases bacteria on skin

Directions

For adults and children of 2 years and over.

Children under 2 years ask a doctor before use.

Allow to dry without wiping.

Warnings

For external use only.

Do not use

over large areas of the body

if you are allergic to any of the ingredients

when using this product,avoid contact with eyes and face.

If contact occurs,flush thoroughly with water.

Stop use and ask a doctor if irritation or rash develops and continues for more than 72 hours.

Keep out of reach of children. If swallowed, get medical help or contact aPoisonControlCenter right away.

Inactive Ingredients

water,sodium lauryl sulfate,fragrance,2-bromo-2-nitropropane-1,3-diol,aloe barbadensis leaf extract,disodium EDTA,trithanolamine ,glycerin,tocopheryl acetate